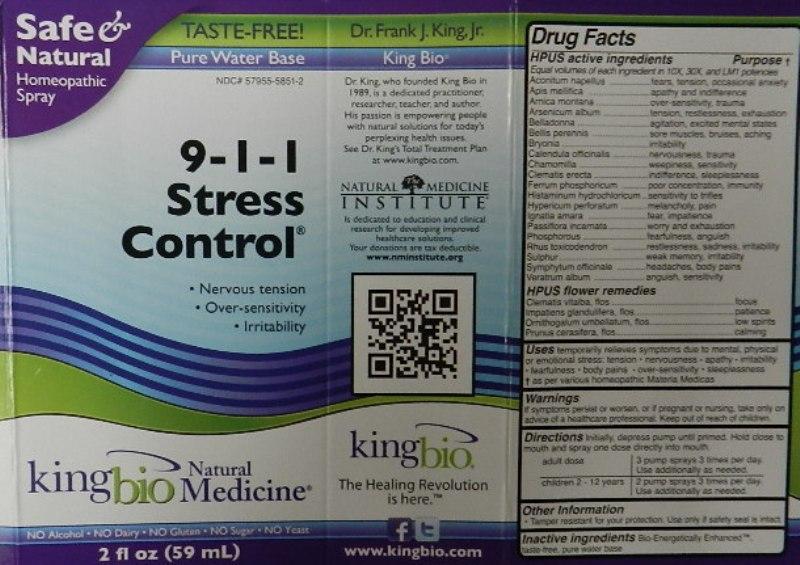 DRUG LABEL: 9-1-1 Stress Control
NDC: 57955-5851 | Form: LIQUID
Manufacturer: King Bio Inc.
Category: homeopathic | Type: HUMAN OTC DRUG LABEL
Date: 20120830

ACTIVE INGREDIENTS: ACONITUM NAPELLUS 10 [hp_X]/59 mL; APIS MELLIFERA 10 [hp_X]/59 mL; ARNICA MONTANA 10 [hp_X]/59 mL; ARSENIC TRIOXIDE 10 [hp_X]/59 mL; ATROPA BELLADONNA 10 [hp_X]/59 mL; BELLIS PERENNIS 10 [hp_X]/59 mL; BRYONIA ALBA ROOT 10 [hp_X]/59 mL; CALENDULA OFFICINALIS FLOWERING TOP 10 [hp_X]/59 mL; MATRICARIA RECUTITA 10 [hp_X]/59 mL; CLEMATIS RECTA FLOWERING TOP 10 [hp_X]/59 mL; FERROSOFERRIC PHOSPHATE 10 [hp_X]/59 mL; HISTAMINE DIHYDROCHLORIDE 10 [hp_X]/59 mL; HYPERICUM PERFORATUM 10 [hp_X]/59 mL; STRYCHNOS IGNATII SEED 10 [hp_X]/59 mL; PASSIFLORA INCARNATA FLOWER 10 [hp_X]/59 mL; PHOSPHORUS 10 [hp_X]/59 mL; TOXICODENDRON PUBESCENS LEAF 10 [hp_X]/59 mL; SULFUR 10 [hp_X]/59 mL; COMFREY ROOT 10 [hp_X]/59 mL; VERATRUM ALBUM ROOT 10 [hp_X]/59 mL; CLEMATIS VITALBA FLOWER 10 [hp_X]/59 mL; IMPATIENS GLANDULIFERA FLOWER 10 [hp_X]/59 mL; ORNITHOGALUM UMBELLATUM FLOWERING TOP 10 [hp_X]/59 mL; PRUNUS CERASIFERA FLOWER 10 [hp_X]/59 mL
INACTIVE INGREDIENTS: WATER

9-1-1 Stress Control

Active Ingredients

HPUS active ingredients

Equal volumes of each ingredient in 10X, 30X and LM1potencies: Aconitum napellus, Apis mellifica, Arnica montana, Arsenicum album, Belladonna, Bellis perennis, Bryonia, Calendula officinalis, Chamomilla, Clematis erecta, Ferrum phosphoricum, Histaminum hydrochloricum, Hypericum perforatum, Ignatia amara, Passiflora incarnata, Phosphorous, Rhus toxicodendron, Sulphur, Symphytum officinale and Veratrum album.

HPUS flower remedies: Clematis vitalba, flos, Impatiens glandulfera, flos, Ornithogalum Umbellatum, flos and Prunus cerasifera, flos.

Inactive Ingredient

Bio-Energetically Enhanced, taste-free, pure water base.

Purpose

HPUS active ingredients Purpose

Equal volumes of each ingredient in 10X, 30X, and LM1 potencies:

Aconitum napellus...............................................fears, tension, occasional anxiety

Apis mellifica......................................................apathy and indifference

Arnica montana...................................................over-sensitivity, trauma

Arsenicum album.................................................tension, restlessness, exhaustion

Belladonna...........................................................agitation, excited mental states

Bellis perennis......................................................sore muscles, bruises, aching

Bryonia................................................................irritability

Calendula officinalis..............................................nervousness, trauma

Chamomilla .........................................................weepiness, sensitivity

Clematis erecta....................................................indifference, sleeplessness

Ferrum phosphoricum...........................................poor concentration, immunity

Histaminum hydrochloricum..................................sensitivity to trifles

Hypericum perforatum..........................................melancholy, pain

Ignatia amara.......................................................fear, impatience

Passiflora incarnata..............................................worry and exhaustion

Phosphorous.......................................................fearfulness, anguish

Rhus toxicodendron.............................................restlessness, sadness, irritability

Sulphur...............................................................weak memory, irritability

Symphytum officinale..........................................headaches, body pains

Veratrum album...................................................anguish, sensitivity

HPUS flower remedies:

Clematis vitalba, flos ...........................................focus

Impatiens glandulfera, flos....................................patience

Ornithogalum Umbellatum, flos.............................low spirits

Prunus cerasifera, flos.........................................calming

Warnings

If symptoms persist or worsen, or if pregnant or nursing, take only on advice of a healthcare professional.

Other Information: Tamper resistant for your protection. Use only if safety seal is intact.

Keep out of reach of children.

Dosage and Administration

Directions Initially, depress pump until primed, Hold close to mouth and spray one dose directly into mouth.
Adult dose 3 pump sprays 3 times per day. Use additionally as needed.
Children 2-12 years 2 pump sprays 3 times per day. Use additionally as needed.

Indications and usage

Uses temporarily relieves symptoms due to mental, physical or emotional stress: tension

- nervousness
- apathy
- irritability
- fearfulness
- body pains
- over-sensitivity
- sleeplessness

As per various homeopathic Materia Medicas.

PACKAGE LABEL

King Bio, Inc.

3 Westside Drive

Asheville, NC 28806

Questions? Call 800.543.3245

wwwkingbio.com

Safe and Natural Homeopathic Spray